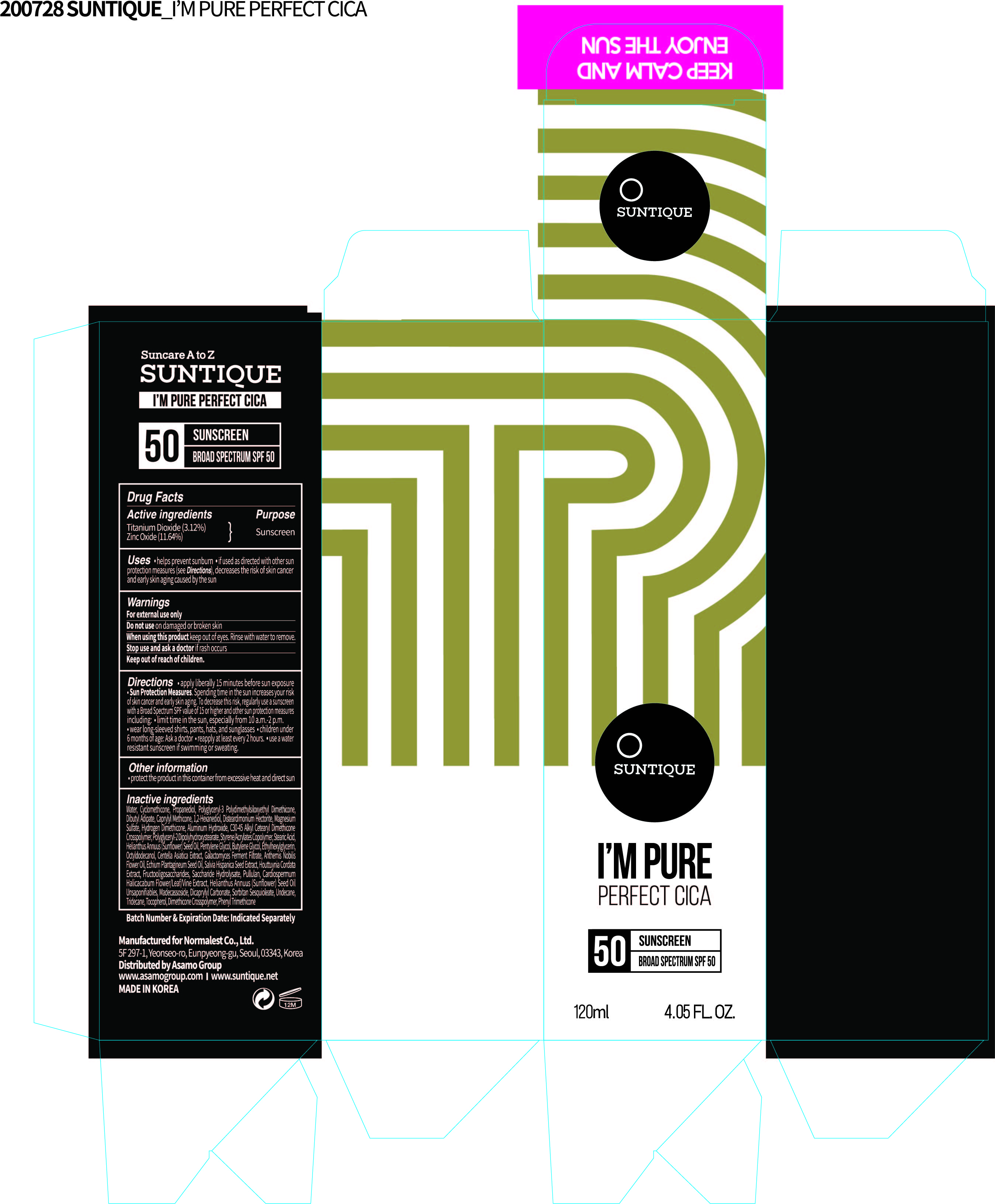 DRUG LABEL: SUNTIQUE IM PURE PERFECT CICA
NDC: 72284-0120 | Form: LOTION
Manufacturer: Normalest Co., Ltd.
Category: otc | Type: HUMAN OTC DRUG LABEL
Date: 20200728

ACTIVE INGREDIENTS: TITANIUM DIOXIDE 3.744 g/120 mL; ZINC OXIDE 13.968 g/120 mL
INACTIVE INGREDIENTS: HOUTTUYNIA CORDATA FLOWERING TOP; INVERT SUGAR; PULLULAN; CARDIOSPERMUM HALICACABUM FLOWERING TOP; DICAPRYLYL CARBONATE; TOCOPHEROL; DISTEARDIMONIUM HECTORITE; POLYGLYCERYL-2 DIPOLYHYDROXYSTEARATE; ECHIUM PLANTAGINEUM SEED OIL; SALVIA HISPANICA SEED; TRIDECANE; MADECASSOSIDE; PROPANEDIOL; DIBUTYL ADIPATE; CAPRYLYL TRISILOXANE; ALUMINUM HYDROXIDE; SORBITAN SESQUIOLEATE; CYCLOMETHICONE; UNDECANE; WATER; 1,2-HEXANEDIOL; MAGNESIUM SULFATE, UNSPECIFIED; PHENYL TRIMETHICONE; STYRENE/ACRYLAMIDE COPOLYMER (MW 500000); STEARIC ACID; SUNFLOWER OIL; PENTYLENE GLYCOL; BUTYLENE GLYCOL; ETHYLHEXYLGLYCERIN; OCTYLDODECANOL; CHAMAEMELUM NOBILE FLOWER OIL

SUNTIQUE I'M PURE PERFECT CICA
120 mL